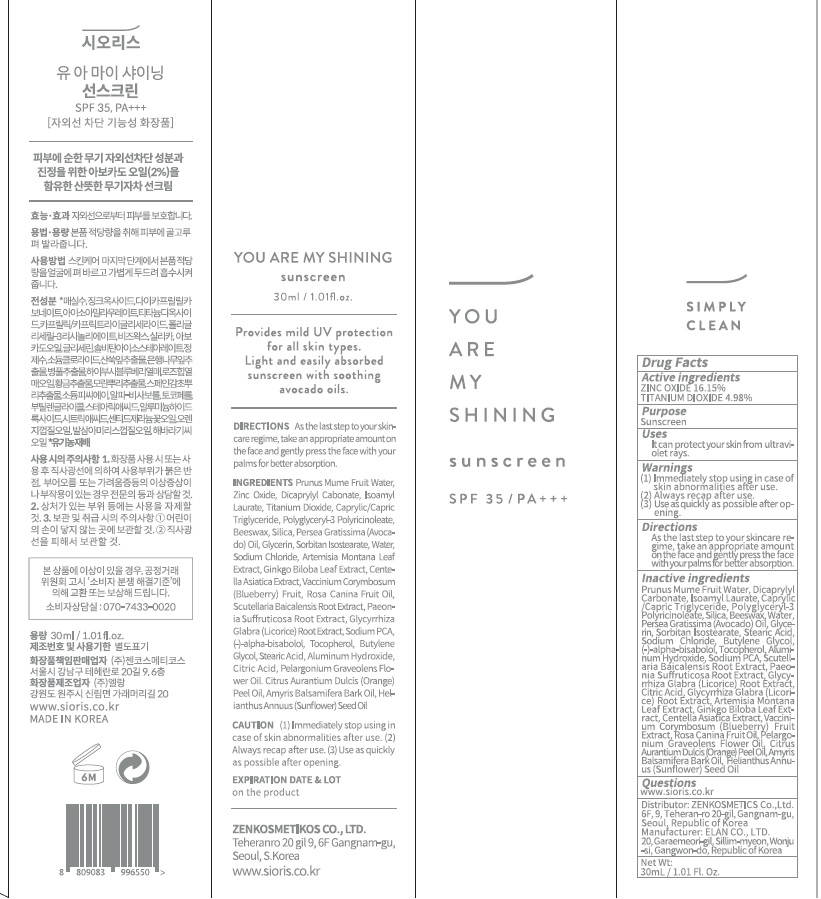 DRUG LABEL: SIORISYOU ARE MY SHINING SUNSCREEN
NDC: 73495-020 | Form: CREAM
Manufacturer: Zenkosmetikos Co., Ltd.
Category: otc | Type: HUMAN OTC DRUG LABEL
Date: 20191224

ACTIVE INGREDIENTS: ZINC OXIDE 4.84 g/30 mL; TITANIUM DIOXIDE 1.49 g/30 mL
INACTIVE INGREDIENTS: PRUNUS MUME FRUIT OIL; DICAPRYLYL CARBONATE

ACTIVE INGREDIENT

Active ingredients: ZINC OXIDE 16.15%, TITANIUM DIOXIDE 5.10%

INACTIVE INGREDIENT

Inactive ingredients:

Prunus Mume Fruit Water, Dicaprylyl Cabonate, Isoamyl Laurate, Caprylic/Capric Triglyceride, Polyglyceryl-3 Ricinoleate, Bees- wax, Silica, Persea Gratissima (Avocado) Oil, Glycerin, Sorbitan Isostearate, Water, Sodium Chloride, Artemisia Montana Leaf Extract, Ginkgo Biloba Leaf Extract, Centella Asiatica Extract, Vaccinium Corymbosum (Blueberry) Fruit, Rosa Canina Fruit Oil, Scutellaria Baicalensis Root Extract, Paeonia Suﬀruticosa Root Extract, Glycyrrhiza Glabra (Licorice) Root Extract, Sodium PCA, (-)-alpha-bisabolol, Tocopherol, Butylene Glycol, Stearic Acid, Aluminum Hydroxide, Citric Acid, Pelargonium Graveolens Flower Oil. Citrus Aurantium Dulcis (Orange) Peel Oil, Amyris Balsamifera Bark Oil, Helianthus Annuus (Sunﬂower) Seed Oil

PURPOSE

Purpose: Sunscreen

WARNINGS

(1) Immediately stop using in case of skin abnormalities after use.
(2) Always recap after use.
(3) Use as quickly as possible after opening.

DESCRIPTION

Uses:
■ It can protect your skin from ultraviolet rays.

Directions:
■ As the last step to your skincare regime, take an appropriate amount on the face and gently press the face with your palms for better absorption.